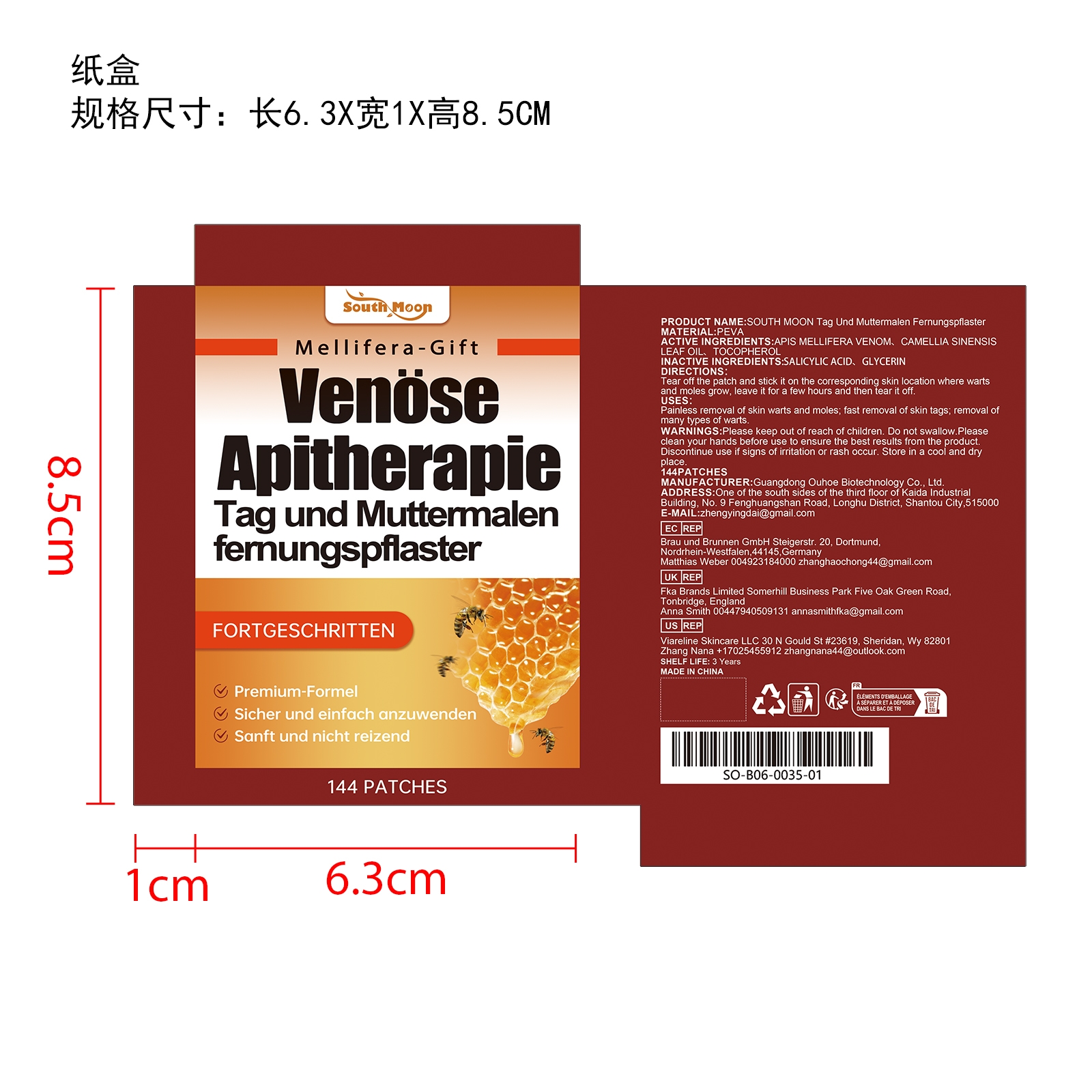 DRUG LABEL: SOUTH MOON Tag Und Muttermalen Fernungspflaster
NDC: 84744-051 | Form: PATCH
Manufacturer: Guangdong Ouhoe Biotechnology Co., Ltd.
Category: otc | Type: HUMAN OTC DRUG LABEL
Date: 20241021

ACTIVE INGREDIENTS: TOCOPHEROL 21.6 mg/144 mg; TEA LEAF OIL 14.4 mg/144 mg; APIS MELLIFERA VENOM 43.2 mg/144 mg
INACTIVE INGREDIENTS: SALICYLIC ACID 21.6 mg/144 mg; GLYCERIN 36 mg/144 mg

ACTIVE INGREDIENTS

APIS MELLIFERA VENOM,TEA LEAF OIL,TOCOPHEROL

purpose

Painless removal of skin warts and moles; fast removal of skin tags; removal of many types of warts.

use

Tear off the patch and stick it on the corresponding skin location where warts and moles grow, leave it for a few hours and then tear it off.

WARNINGS

Please keep out of reach of children. Do not swallow.Pleasel clean your hands before use to ensure the best results from the product. Discontinue use if signs of irritation or rash occur. Store in a cool and dry place.

Do not use

Discontinue use if signs of irritation or rash occur.

Stop use

Discontinue use if signs of irritation or rash occur.

KEEP OUT OF REACH OF CHILDREN

Please keep out of reach of children. Do not swallow.

STORAGE AND HANDLING

Store in a cool and dry place.

INACTIVE INGREDIENT

SALICYLIC ACID、GLYCERIN